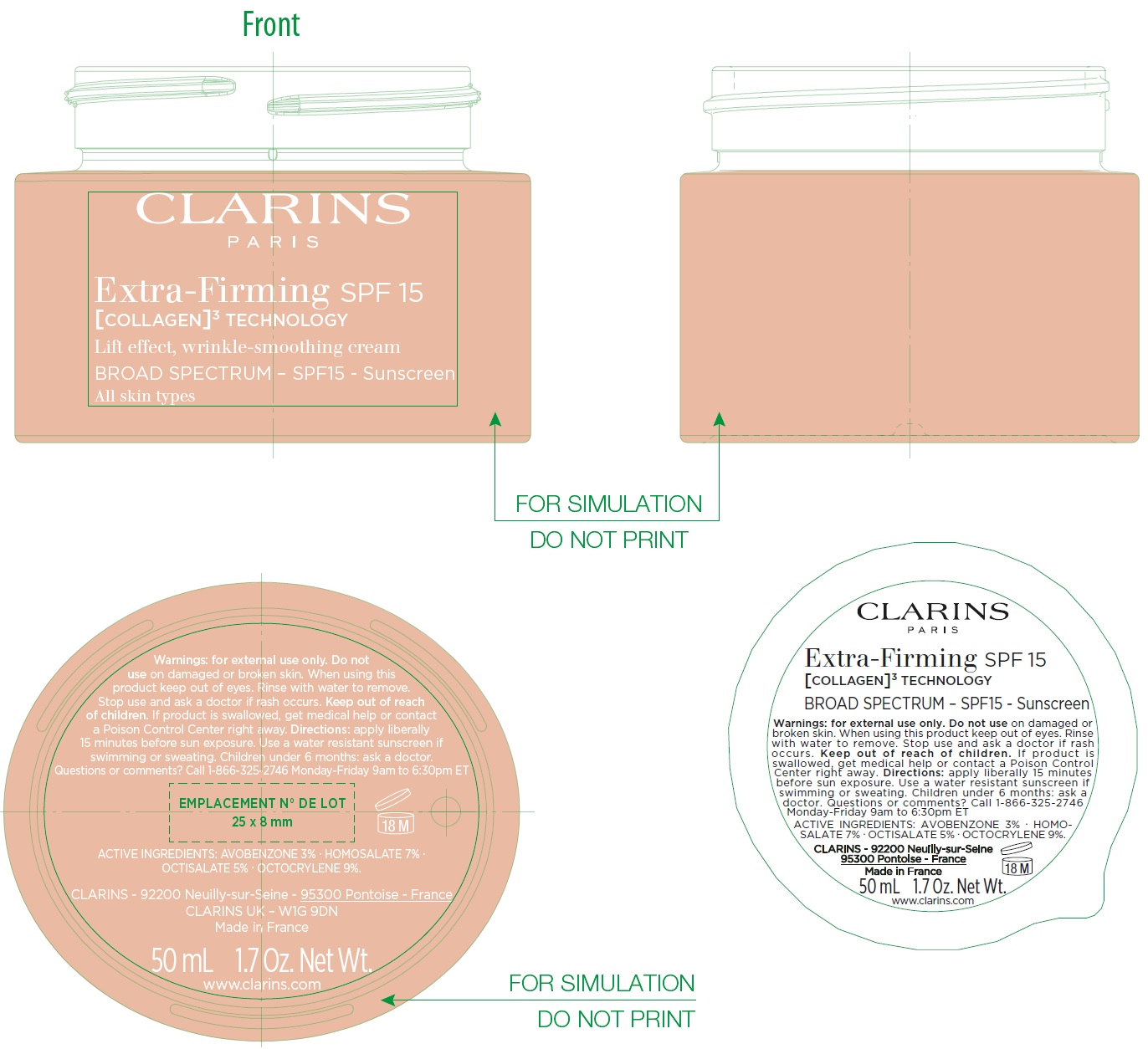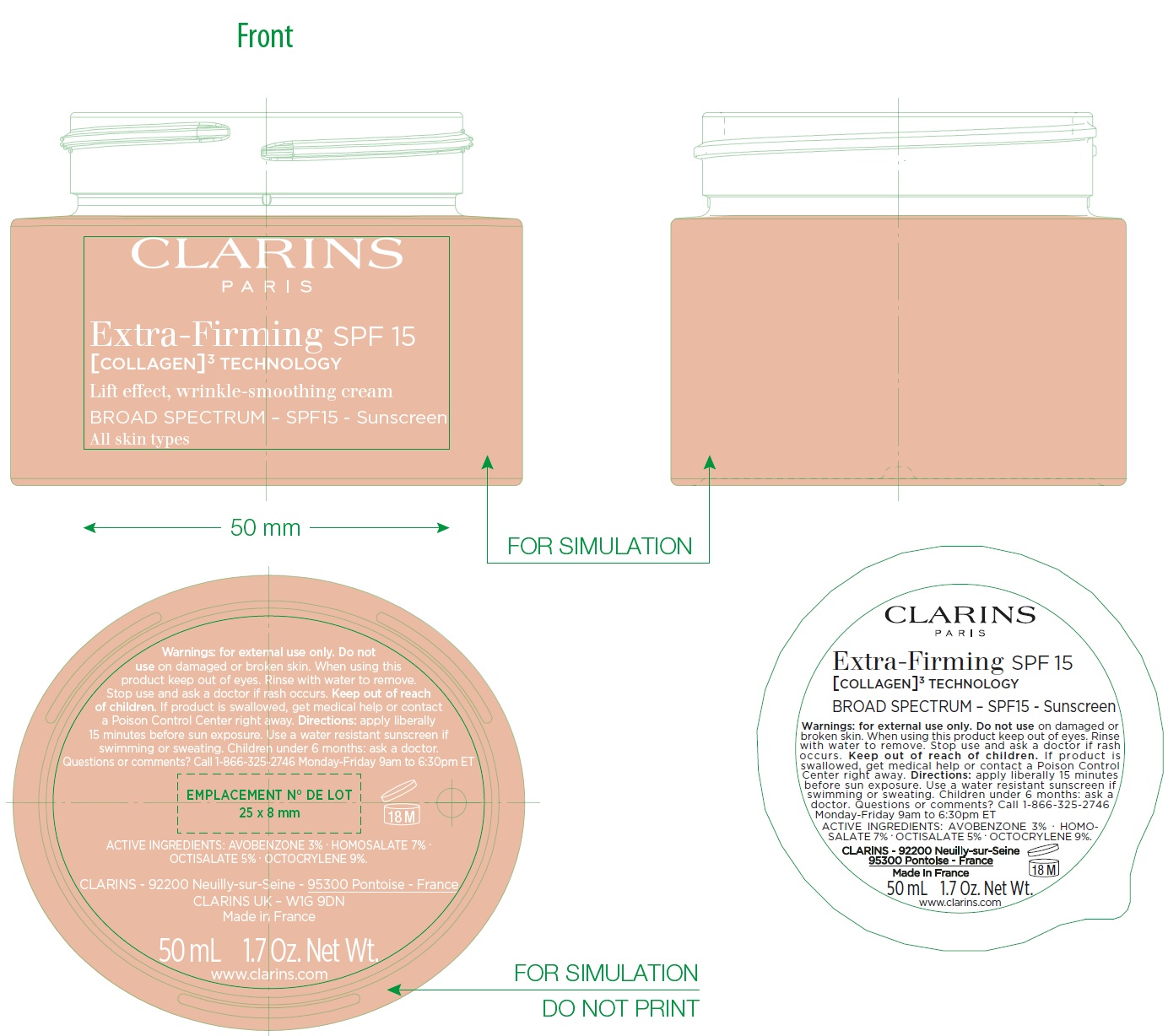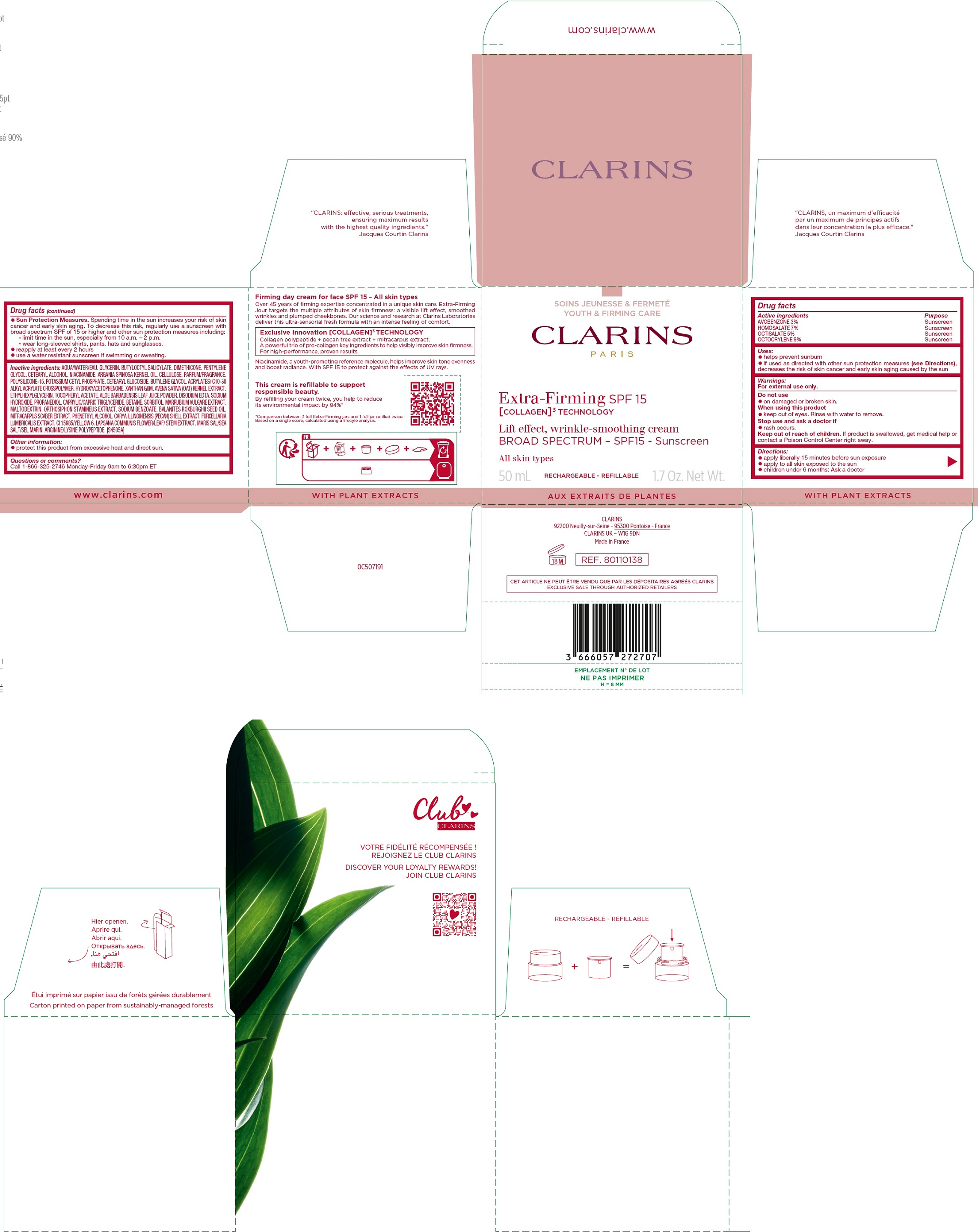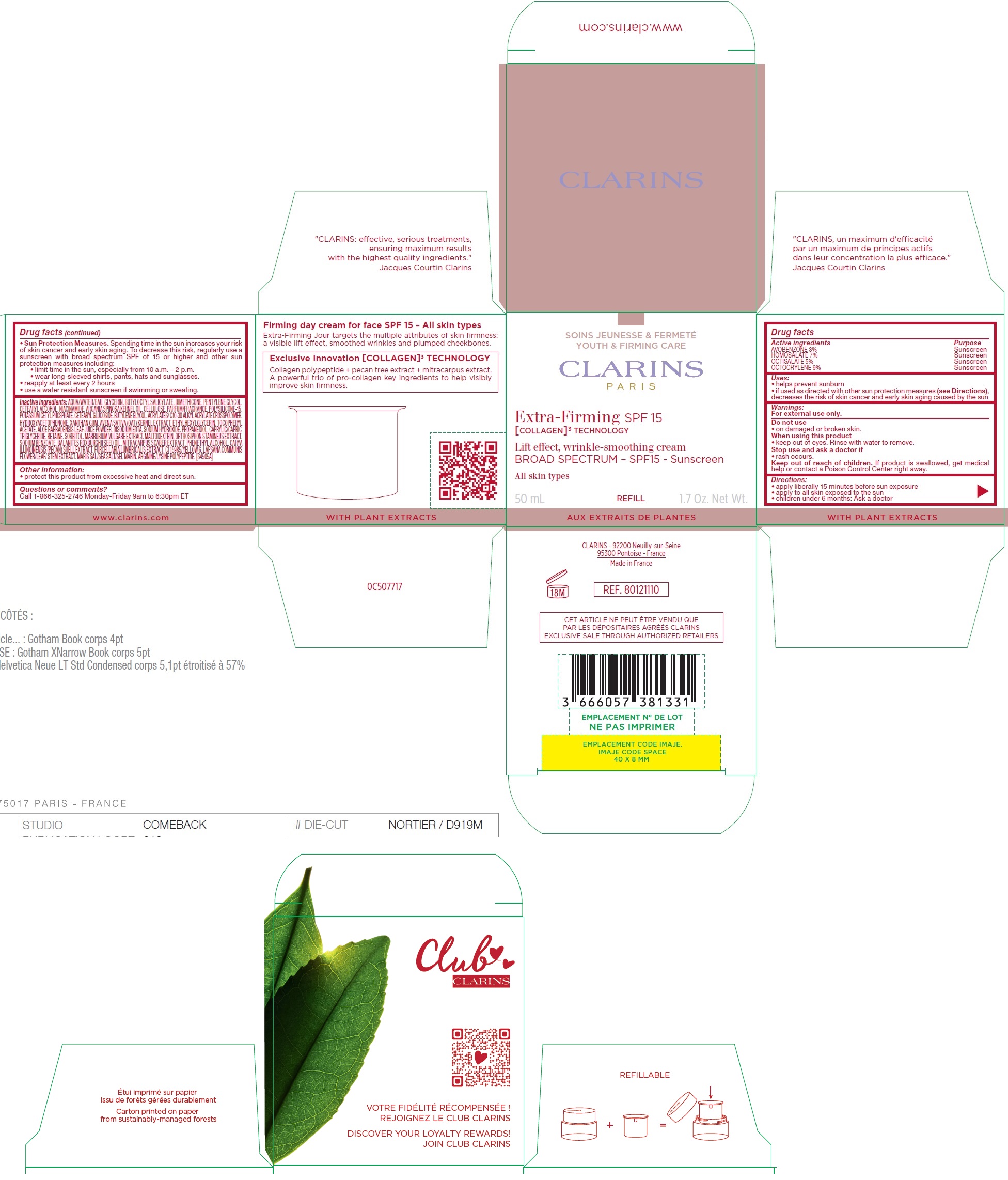 DRUG LABEL: CLARINS Extra Firming Sunscreen SPF 15
NDC: 58668-9818 | Form: CREAM
Manufacturer: Laboratoires Clarins
Category: otc | Type: HUMAN OTC DRUG LABEL
Date: 20250908

ACTIVE INGREDIENTS: AVOBENZONE 30 mg/1 mL; HOMOSALATE 70 mg/1 mL; OCTISALATE 50 mg/1 mL; OCTOCRYLENE 90 mg/1 mL
INACTIVE INGREDIENTS: WATER; GLYCERIN; BUTYLOCTYL SALICYLATE; DIMETHICONE; PENTYLENE GLYCOL; CETOSTEARYL ALCOHOL; NIACINAMIDE; ARGANIA SPINOSA KERNEL OIL; POWDERED CELLULOSE; POLYSILICONE-15; POTASSIUM CETYL PHOSPHATE; CETEARYL GLUCOSIDE; BUTYLENE GLYCOL; HYDROXYACETOPHENONE; XANTHAN GUM; OAT; ETHYLHEXYLGLYCERIN; .ALPHA.-TOCOPHEROL ACETATE; ALOE VERA LEAF JUICE; EDETATE DISODIUM; SODIUM HYDROXIDE; PROPANEDIOL; MEDIUM-CHAIN TRIGLYCERIDES; BETAINE; SORBITOL; HOREHOUND; MALTODEXTRIN; SODIUM BENZOATE; BALANITES ROXBURGHII SEED OIL; PHENETHYL ALCOHOL; FURCELLERAN; FD&C YELLOW NO. 6; LAPSANA COMMUNIS FLOWERING TOP; ARGININE

CLARINS – Extra Firming Sunscreen SPF 15

Active ingredients

AVOBENZONE 3%
HOMOSALATE 7%
OCTISALATE 5%
OCTOCRYLENE 9%

Purpose

Sunscreen

Uses:

- helps prevent sunburn
- if used as directed with other sun protection measures (see Directions), decreases the risk of skin cancer and early skin aging caused by the sun

Warnings:

For external use only.

Do not use

- on damaged or broken skin.

When using this product

- keep out of eyes. Rinse with water to remove.

Stop use and ask a doctor if

- rash occurs.

Keep out of reach of children.

If product is swallowed, get medical help or contact a Poison Control Center right away.

Directions:

- apply liberally 15 minutes before sun exposure
- apply to all skin exposed to the sun
- children under 6 months: Ask a doctor
- Sun Protection Measures.Spending time in the sun increases your risk of skin cancer and early skin aging. To decrease this risk, regularly use a sunscreen with broad spectrum SPF of 15 or higher and other sun protection measures including:
- limit time in the sun, especially from 10 a.m. – 2 p.m.
- wear long-sleeved shirts, pants, hats and sunglasses.
- reapply at least every 2 hours
- use a water resistant sunscreen if swimming or sweating.

Inactive ingredients:

AQUA/WATER/EAU. GLYCERIN. BUTYLOCTYL SALICYLATE. DIMETHICONE. PENTYLENE GLYCOL. CETEARYL ALCOHOL. NIACINAMIDE. ARGANIA SPINOSA KERNEL OIL. CELLULOSE. PARFUM/FRAGRANCE. POLYSILICONE-15. POTASSIUM CETYL PHOSPHATE. CETEARYL GLUCOSIDE. BUTYLENE GLYCOL. ACRYLATES/ C10-30 ALKYL ACRYLATE CROSSPOLYMER. HYDROXYACETOPHENONE. XANTHAN GUM. AVENA SATIVA (OAT) KERNEL EXTRACT. ETHYLHEXYLGLYCERIN. TOCOPHERYL ACETATE. ALOE BARBADENSIS LEAF JUICE POWDER. DISODIUM EDTA. SODIUM HYDROXIDE. PROPANEDIOL. CAPRYLIC/CAPRIC TRIGLYCERIDE. BETAINE. SORBITOL. MARRUBIUM VULGARE EXTRACT. MALTODEXTRIN. ORTHOSIPHON STAMINEUS EXTRACT. SODIUM BENZOATE. BALANITES ROXBURGHII SEED OIL. MITRACARPUS SCABER EXTRACT. PHENETHYL ALCOHOL. CARYA ILLINOINENSIS (PECAN) SHELL EXTRACT. FURCELLARIA LUMBRICALIS EXTRACT. CI 15985/YELLOW 6. LAPSANA COMMUNIS FLOWER/LEAF/ STEM EXTRACT. MARIS SAL/SEA SALT/SEL MARIN. ARGININE/LYSINE POLYPEPTIDE. [S4505A]

Other information:

- protect this product from excessive heat and direct sun.

Questions or comments?

Call 1-866-325-2746 Monday-Friday 9am to 6:30pm ET